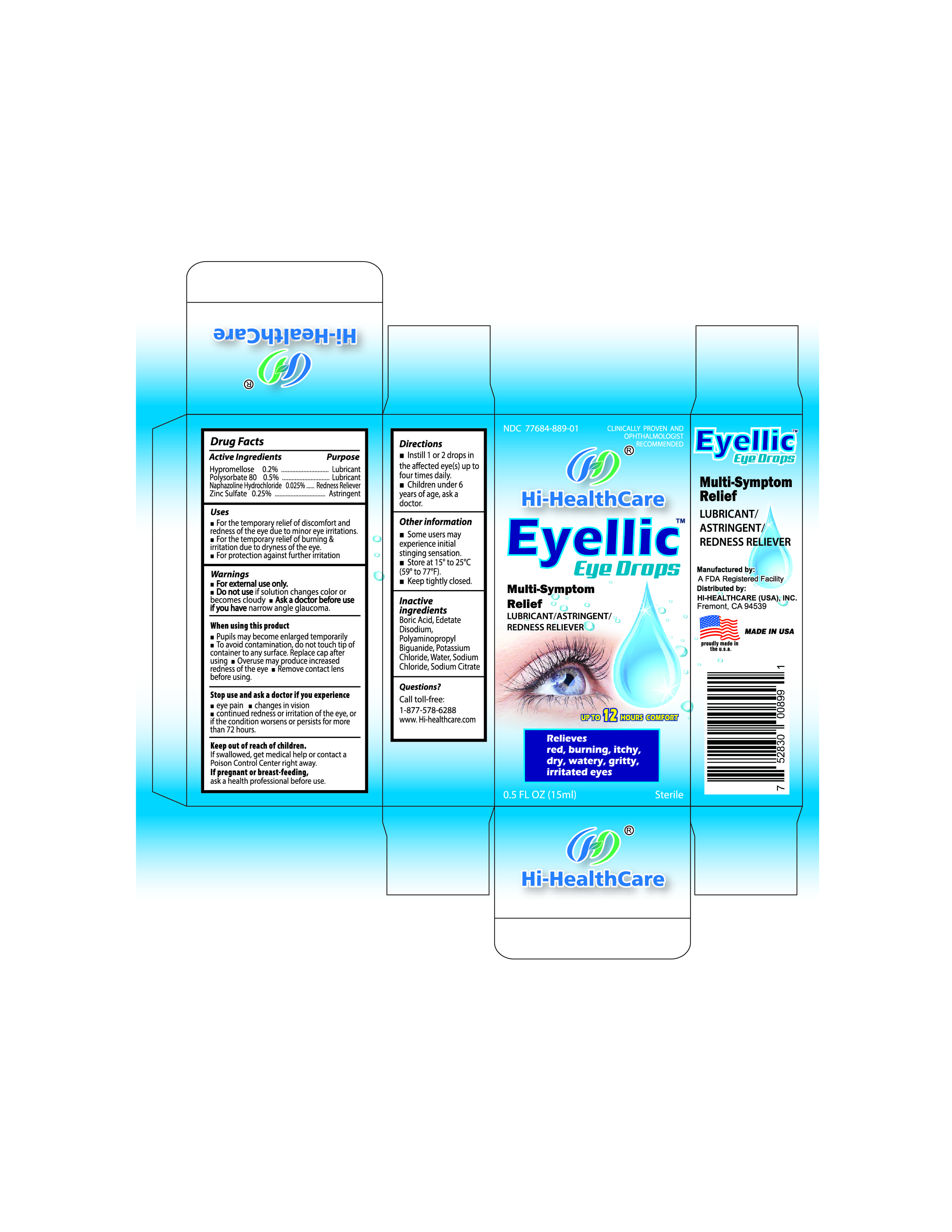 DRUG LABEL: Eyellic Eye Drops (Sterile)
NDC: 77684-899 | Form: SOLUTION/ DROPS
Manufacturer: Hi-Healthcare Inc
Category: otc | Type: HUMAN OTC DRUG LABEL
Date: 20200522

ACTIVE INGREDIENTS: HYPROMELLOSES 0.2 g/100 mL; POLYSORBATE 80 0.5 g/100 mL; NAPHAZOLINE HYDROCHLORIDE 0.025 g/100 mL; ZINC SULFATE 0.25 g/100 mL
INACTIVE INGREDIENTS: BORIC ACID; EDETATE DISODIUM; POLYAMINOPROPYL BIGUANIDE HYDROCHLORIDE; POTASSIUM CHLORIDE; WATER; SODIUM CHLORIDE; SODIUM CITRATE

Hi-Healthcare Inc

Active Ingredients

Hypromelloses 0.2%
Polysorbate 80 0.5%
Naphazoline Hydrochloride 0.025%
Zinc Sulfate 0.25%

Purpose

Hypromelloses Lubricant
Polysorbate 80 Lubricant
Naphazoline Hydrochloride Redness Reliever
Zinc Sulfate Astringent

Uses

- For the temporary relief of discomfort and redness of the eye due to minor eye irritations.
- For the temporary relief of burning & irritation due to dryness of the eye.
- For protection against further irritation.

Directions

• Instill 1 or 2 drops in the affected eye(s) up to four times daily.
• Children under 6 years of age, ask a doctor.

Warnings

• For external use only.
• Do not use if solution changes color or becomes cloudy.
• Ask a doctor before use if you have narrow angle glaucoma.

When using this product

• Pupils may become enlarged temporarily.
• To avoid contamination, do not touch tip of container to any surface. Replace cap after using.
• Overuse may produce increased redness of the eye.
• Remove contact lens before using.

Stop use and ask a doctor if you experience

• eye pain.
• changes in vision.
• continued redness or irritation of the eye, or if the condition worsens or persists for more than 72 hours.

Keep out of reach of children.

If swallowed, get medical help or contact a Poison Control Center right away.

Other information

• Some users may experience initial stinging sensation.
• Store at 15° to 25°C (59° to 77°F).
• Keep tightly closed.
• Use before expiration date marked on the carton and bottle.

Questions or Comments?

Contact Hi-Healthcare, Inc.
1-877-578-6288
www.hi-healthcare.com

Distributed by Hi-Healthcare Inc.

Made in USA

Inactive ingredients

Boric Acid, Edetate Disodium, Polyaminopropyl Biguanide, Potassium Chloride, Water, Sodium Chloride, Sodium Citrate